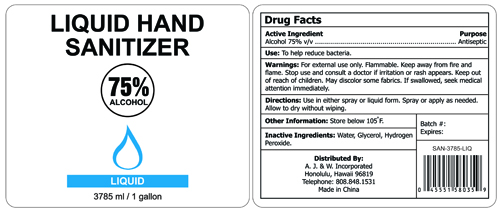 DRUG LABEL: Hand Sanitizer
NDC: 74839-003 | Form: LIQUID
Manufacturer: A. J. & W. Incorporated
Category: otc | Type: HUMAN OTC DRUG LABEL
Date: 20220118

ACTIVE INGREDIENTS: ALCOHOL 75 mL/100 mL
INACTIVE INGREDIENTS: GLYCERIN 1.45 mL/100 mL; HYDROGEN PEROXIDE 0.125 mL/100 mL; WATER

Active Ingredient(s)

Alcohol 75% v/v.

Purpose

Antiseptic

Use

Hand Sanitizer to help reduce bacteria that potentially can cause disease. For use when soap and water are not available.

Warnings

For external use only. Flammable. Keep away from heat or flame

Do not use

- On children less than 2 months of age
- On open skin wounds

When using this product keep out of eyes, ears, and mouth. In case of contact with eyes, rinse eyes thoroughly with water.
Stop use and ask a doctor if irritation or rash occurs.

These may be signs of a serious condition.
Keep out of reach of children.

If swallowed, get medical help or contact a Poison Control Center right away.

Stop use and ask a doctor if irritation or rash occurs. These may be signs of a serious condition.

Keep out of reach of children. If swallowed, get medical help or contact a Poison Control Center right away.

Directions

- Place enough product on hands to cover all surfaces. Rub hands together until dry.
- Supervise children under 6 years of age when using this product to avoid swallowing.

Other information

- Store between 15-30C (59-86F)
- Avoid freezing and excessive heat above 40C (104F)

Inactive ingredients

Water (aqua), Glycerin, Hydrogen peroxide

Package Label - Principal Display Panel

3785 mL NDC: 74839-003-37